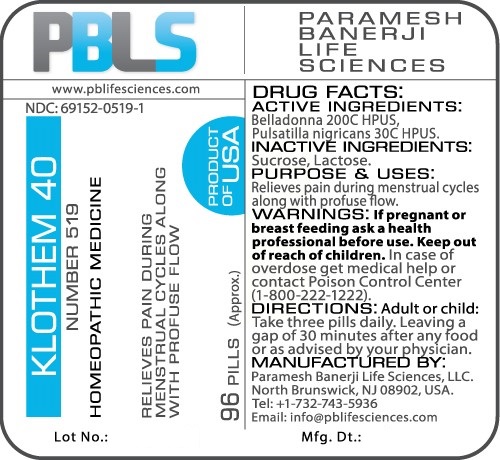 DRUG LABEL: Klothem (Number 519)
NDC: 69152-0519 | Form: PELLET
Manufacturer: Paramesh Banerji Life Sciences LLC
Category: homeopathic | Type: HUMAN OTC DRUG LABEL
Date: 20170215

ACTIVE INGREDIENTS: PULSATILLA PRATENSIS 30 [hp_C]/1 1; ATROPA BELLADONNA 200 [hp_C]/1 1
INACTIVE INGREDIENTS: SUCROSE; LACTOSE

DRUG FACTS: Active Ingredients

Belladonna 200C HPUS, Pulsatilla nigricans 30C HPUS

Inactive Ingredients

Sucrose, Lactose

Purpose

Relieves pain during menstrual cycles with profuse flow

Uses

Relieves pain during menstrual cycles with profuse flow

Warnings

If pregnant or breast feeding ask a health professional before use.

Keep out of reach of children. In case of overdose, get medical help or contact a Poison Control Center (1-800-222-1222) right away.

Direction

Adult or child: Take three pills daily. Leaving a gap of 30 minutes after any food or as advised by your physician.

Manufactured by

Paramesh Banerji Life Sciences, LLC.

North Brunswick, NJ 08902, USA.

Tel: +1-732-743-5936

Email: info@pblifesciences.com

Principal Display Panel

NDC: 69152-0519-1

Klothem 40

Number 519

Homeopathic Medicine

Relieves pain during menstrual cycles with profuse flow

96 Pills (Approx.)

Product of USA